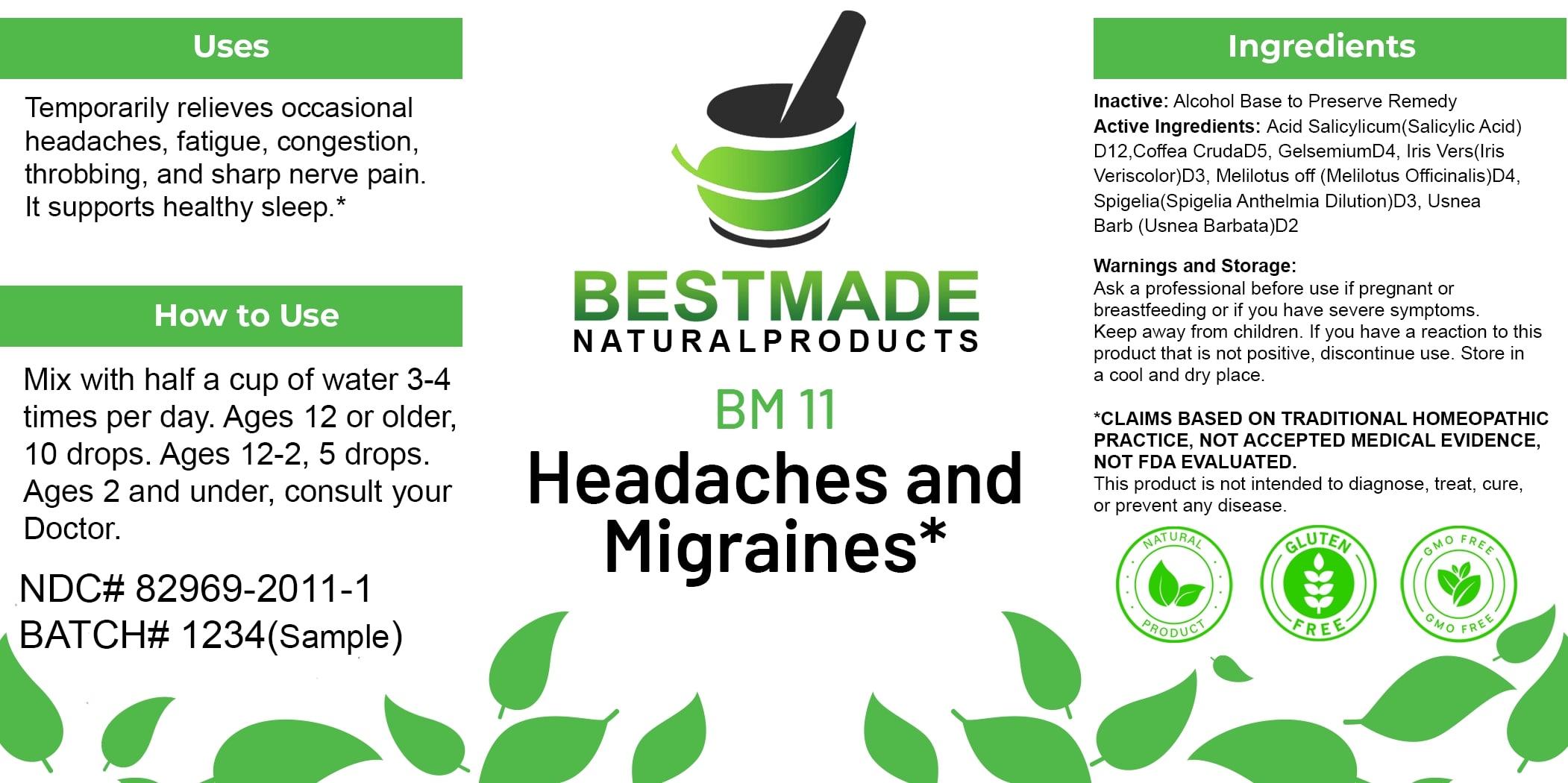 DRUG LABEL: Bestmade Natural Products BM11
NDC: 82969-2011 | Form: LIQUID
Manufacturer: Bestmade Natural Products
Category: homeopathic | Type: HUMAN OTC DRUG LABEL
Date: 20250122

ACTIVE INGREDIENTS: IRIS VERSICOLOR ROOT 30 [hp_C]/30 [hp_C]; ATROPA BELLADONNA 30 [hp_C]/30 [hp_C]; ARABICA COFFEE BEAN 30 [hp_C]/30 [hp_C]; GELSEMIUM SEMPERVIRENS ROOT 30 [hp_C]/30 [hp_C]; MELILOTUS OFFICINALIS TOP 30 [hp_C]/30 [hp_C]; USNEA BARBATA 30 [hp_C]/30 [hp_C]; SALICYLIC ACID 30 [hp_C]/30 [hp_C]; SPIGELIA ANTHELMIA 30 [hp_C]/30 [hp_C]
INACTIVE INGREDIENTS: ALCOHOL 30 [hp_C]/30 [hp_C]

BM11

DOSAGE AND ADMINISTRATION

How to Use

Mix with half a cup of water 3-4 times per day.

Ages 12 or older: 10 drops
Ages 2-12: 5 drops
Ages 2 and under: Consult your doctor.

INACTIVE INGREDIENT

Ingredients

Inactive: Alcohol Base to Preserve Remedy

Uses

Temporarily relieves occasional headaches, fatigue, congestion, throbbing, and sharp nerve pain. It supports healthy sleep.*

*CLAIMS BASED ON TRADITIONAL HOMEOPATHIC PRACTICE, NOT ACCEPTED MEDICAL EVIDENCE, NOT FDA EVALUATED.
This product is not intended to diagnose, treat, cure, or prevent any disease.

Active Ingredients:

Acid Salicylicum (Salicylic Acid) D12
Coffea Cruda D5
Gelsemium D4
Iris Vers (Iris Versicolor) D3
Melilotus Off (Melilotus Officinalis) D4
Spigelia (Spigelia Anthelmia Dilution) D3
Usnea Barb (Usnea Barbata) D2

KEEP OUT OF REACH OF CHILDREN

Warnings and Storage

Ask a professional before use if pregnant or breastfeeding or if you have severe symptoms. Keep away from children. If you have a reaction to this product that is not positive, discontinue use. Store in a cool and dry place.

Uses

Temporarily relieves occasional headaches, fatigue, congestion, throbbing, and sharp nerve pain. It supports healthy sleep.*

*CLAIMS BASED ON TRADITIONAL HOMEOPATHIC PRACTICE, NOT ACCEPTED MEDICAL EVIDENCE, NOT FDA EVALUATED.
This product is not intended to diagnose, treat, cure, or prevent any disease.

Warnings and Storage

Ask a professional before use if pregnant or breastfeeding or if you have severe symptoms. Keep away from children. If you have a reaction to this product that is not positive, discontinue use. Store in a cool and dry place.

*CLAIMS BASED ON TRADITIONAL HOMEOPATHIC PRACTICE, NOT ACCEPTED MEDICAL EVIDENCE, NOT FDA EVALUATED.
This product is not intended to diagnose, treat, cure, or prevent any disease.

Entire package label